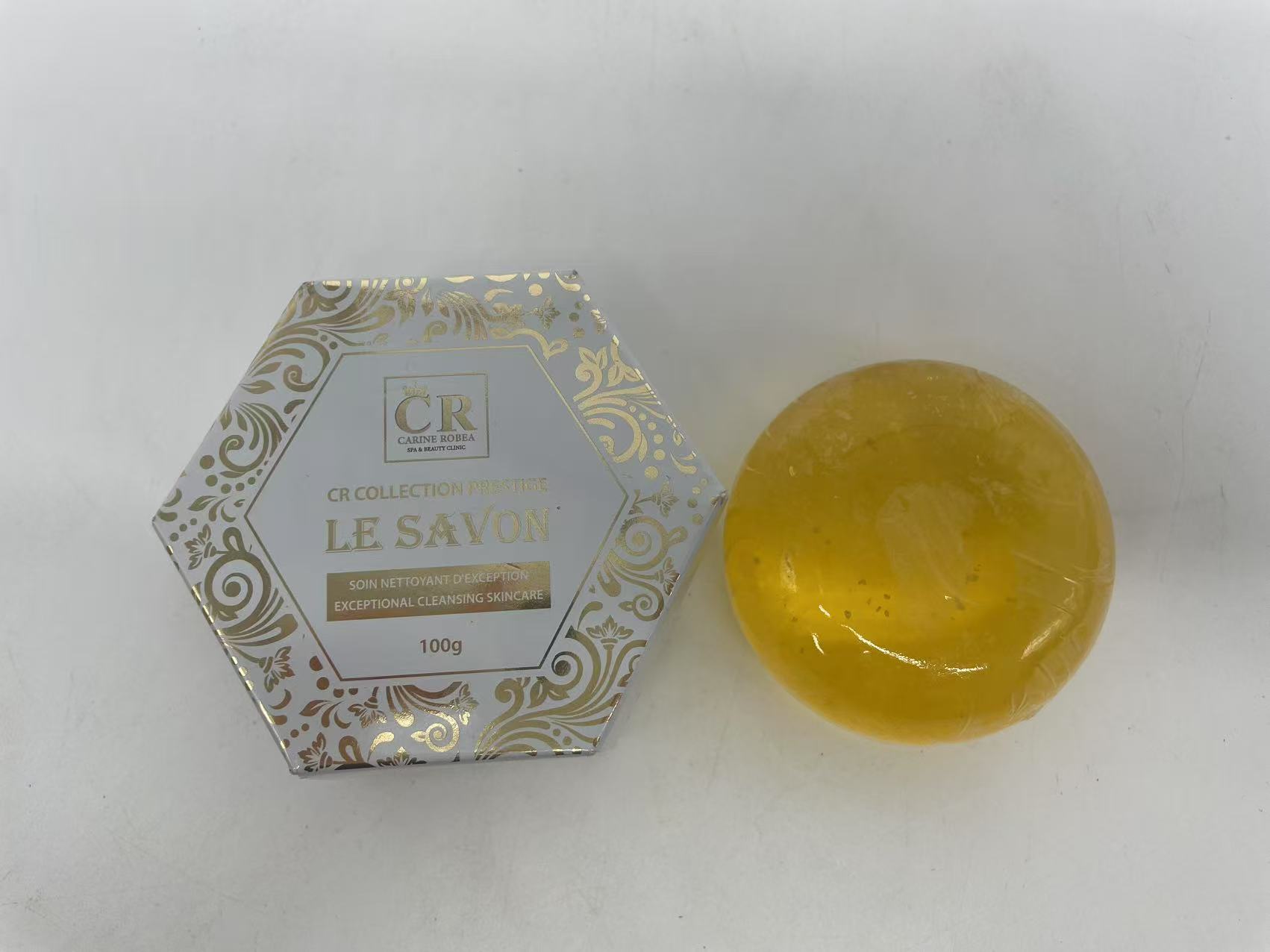 DRUG LABEL: CRSoap
NDC: 84423-082 | Form: SOAP
Manufacturer: Guangzhou Kadiya Biotechnology Co., Ltd.
Category: otc | Type: HUMAN OTC DRUG LABEL
Date: 20250716

ACTIVE INGREDIENTS: ARBUTIN 2 g/100 g; TURMERIC 0.5 g/100 g; NIACINAMIDE 3 g/100 g
INACTIVE INGREDIENTS: WATER; PALM OIL; GINGER; GLYCERIN; SODIUM HYDROXIDE; COCONUT OIL; BUTYROSPERMUM PARKII (SHEA) BUTTER; HONEY

PURPOSE

For facial skin cleansing, exfoliation，Acne and moisturization

INACTIVE INGREDIENT

GLYCERIN
WATER
Coconut oil
Palm oil
Sodium hydroxide
BUTYROSPERMUMPARKII(SHEA)BUTTER
ZINGIBER OFFICINALE (GINGER) ROOT EXTRACT
HONEY

WARNINGS

1、For external use only, avoid contact with eyes when used

2、Keep out of reach of children

INDICATIONS AND USAGE

Soap is a type of cleaning product mainly used for cleansing the skin.

Wet your hands with water, then apply the soap to the palm or rub it directly on the skin to create bubbles. Focus on cleaning the creases of fingers, wrists and other easily overlooked areas. Finally, rinse your hands thoroughly with clean water.

DOSAGE AND ADMINISTRATION

Each time, use approximately 1-2 grams (about the size of a fingertip), and avoid using too much as it may cause difficulties in rinsing.

KEEP OUT OF REACH OF CHILDREN SECTION

ACTIVE INGREDIENT

Arbutine 2%
Nicotinamide3%
Turmeric powder0.5%

PACKAGE LABEL

Active Ingredients
Arbutine 2%
Nicotinamide3%
Turmeric powder0.5%
Uses：
For facial skin cleansing, exfoliation，Acne and moisturization
The storage method：
Store sealed in a cool place and out of sunlight
Warning.
1、For external use only, avoid contact with eyes when used
2、Keep out of reach of children
GLYCERIN
WATER
Coconut oil
Palm oil
Sodium hydroxide
BUTYROSPERMUMPARKII(SHEA)BUTTER
ZINGIBER OFFICINALE (GINGER) ROOT EXTRACT
HONEY